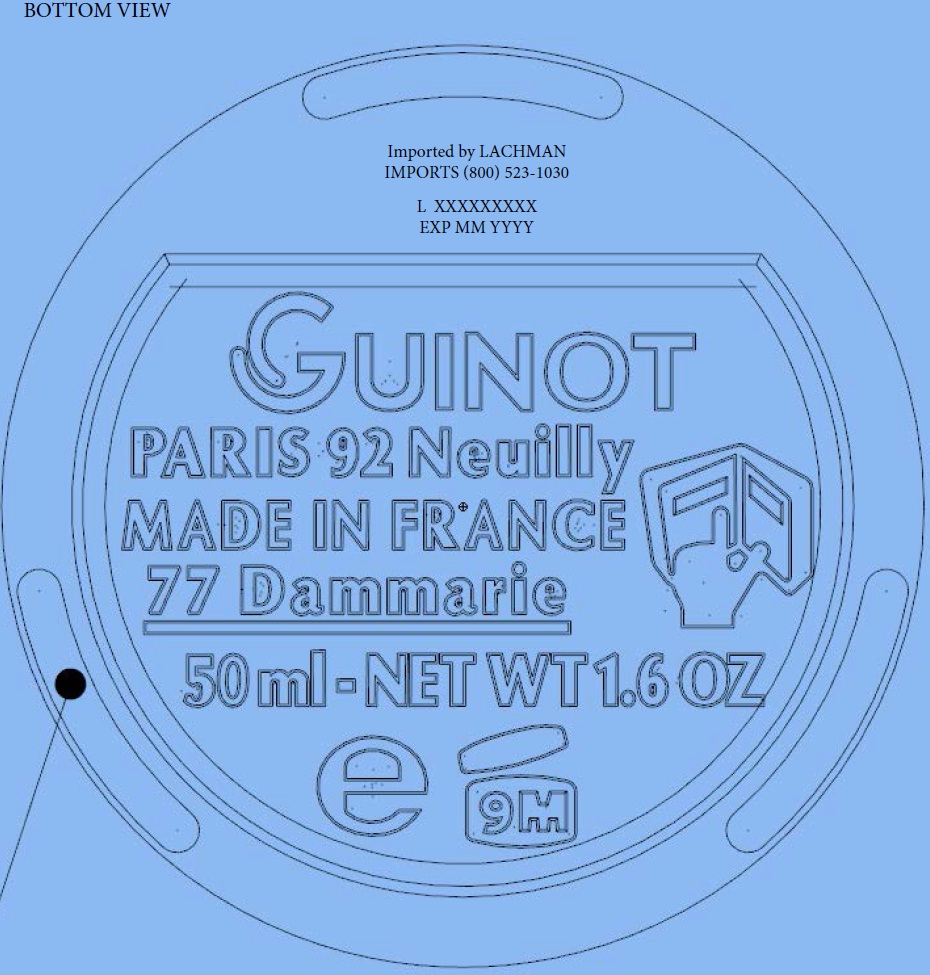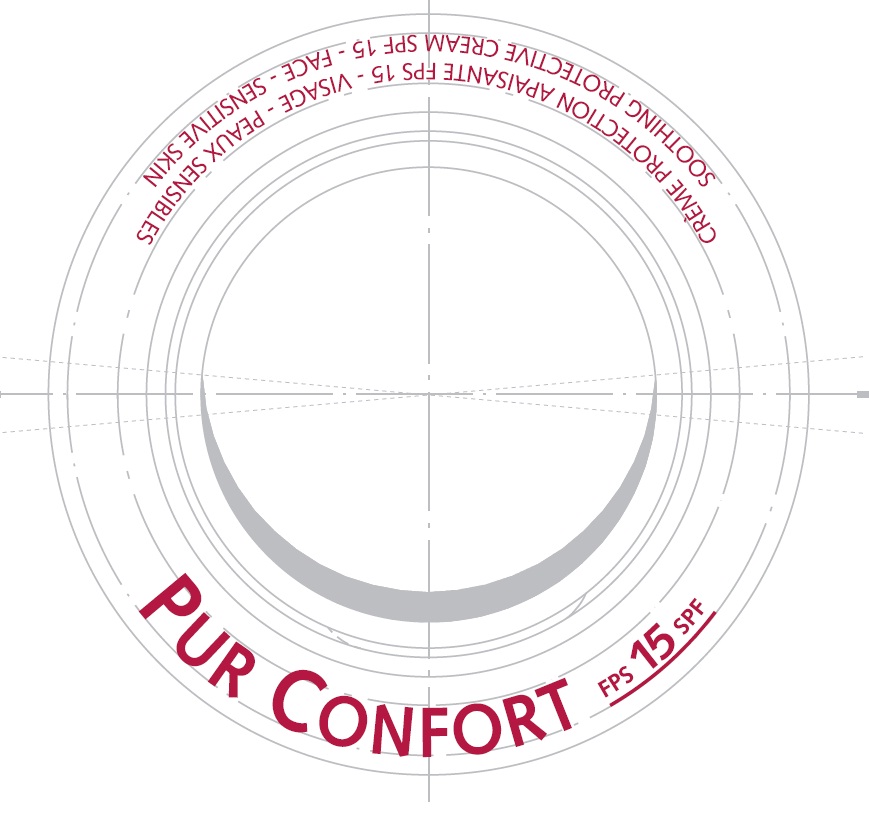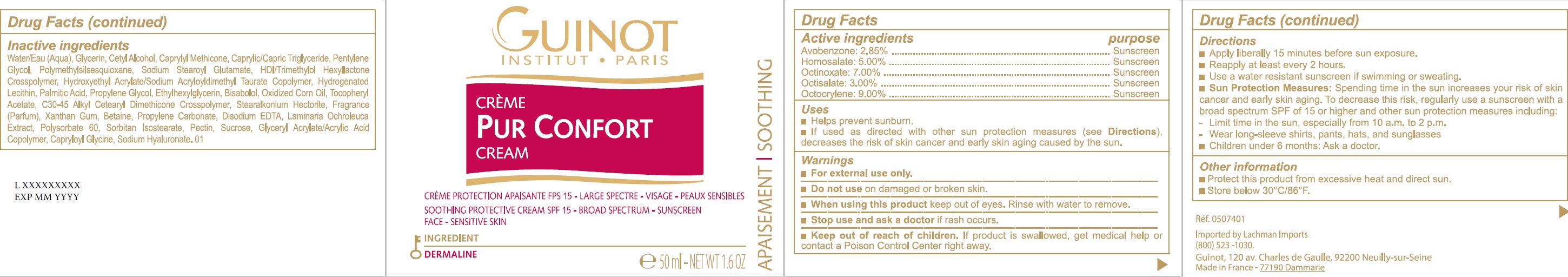 DRUG LABEL: Pur Confort SPF 15
NDC: 54181-015 | Form: CREAM
Manufacturer: Guinot
Category: otc | Type: HUMAN OTC DRUG LABEL
Date: 20260129

ACTIVE INGREDIENTS: AVOBENZONE 28.5 mg/1 mL; HOMOSALATE 50 mg/1 mL; OCTINOXATE 70 mg/1 mL; OCTISALATE 30 mg/1 mL; OCTOCRYLENE 90 mg/1 mL
INACTIVE INGREDIENTS: WATER; GLYCERIN; CETYL ALCOHOL; CAPRYLYL TRISILOXANE; MEDIUM-CHAIN TRIGLYCERIDES; PENTYLENE GLYCOL; POLYMETHYLSILSESQUIOXANE (4.5 MICRONS); SODIUM STEAROYL GLUTAMATE; HEXAMETHYLENE DIISOCYANATE/TRIMETHYLOL HEXYLLACTONE CROSSPOLYMER; HYDROXYETHYL ACRYLATE/SODIUM ACRYLOYLDIMETHYL TAURATE COPOLYMER (100000 MPA.S AT 1.5%); HYDROGENATED SOYBEAN LECITHIN; PALMITIC ACID; PROPYLENE GLYCOL; ETHYLHEXYLGLYCERIN; LEVOMENOL; .ALPHA.-TOCOPHEROL ACETATE; STEARALKONIUM HECTORITE; XANTHAN GUM; BETAINE; PROPYLENE CARBONATE; EDETATE DISODIUM ANHYDROUS; LAMINARIA OCHROLEUCA; POLYSORBATE 60; SORBITAN ISOSTEARATE; PECTIN; SUCROSE; CAPRYLOYL GLYCINE; HYALURONATE SODIUM

Pur Confort SPF 15

Active ingredients

AVOBENZONE: 2.85%

HOMOSALATE: 5.00%

OCTINOXATE: 7.00%

OCTISALATE: 3.00%

OCTOCRYLENE: 9.00%

Purpose

Sunscreen

Uses

- Helps prevent sunburn.
- If used as directed with other sun protection measures (see Directions), decreases the risk of skin cancer and early skin aging caused by the sun.

Warnings

- For external use only.

Do not use

on damaged or broken skin.

When using this product

keep out of eyes. Rinse with water to remove.

Stop use and ask a doctor

if rash occurs.

Keep out of reach of children. If

product is swallowed, get medical help or contact a Poison Control Center right away.

Directions

- Apply liberally 15 minutes before sun exposure.
- Reapply at least every 2 hours.
- Use a water resistant sunscreen if swimming or sweating.
- Spending time in the sun increases your risk of skin cancer and early skin aging. To decrease this risk, regularly use a sunscreen with a broad spectrum SPF of 15 or higher and other sun protection measures including: Sun Protection Measures:
- Limit time in the sun, especially from 10 a.m. to 2 p.m.
- Wear long-sleeve shirts, pants, hats, and sunglasses
- Children under 6 months: Ask a doctor.

Other information

- Protect this product from excessive heat and direct sun.
- Store below 30 C/86 F.oo

Inactive ingredients

Water/Eau (Aqua), Glycerin, Cetyl Alcohol, Caprylyl Methicone, Caprylic/Capric Triglyceride, Pentylene Glycol, Polymethylsilsesquioxane, Sodium Stearoyl Glutamate, HDI/Trimethylol Hexyllactone Crosspolymer, Hydroxyethyl Acrylate/Sodium Acryloyldimethyl Taurate Copolymer, Hydrogenated Lecithin, Palmitic Acid, Propylene Glycol, Ethylhexylglycerin, Bisabolol, Oxidized Corn Oil, Tocopheryl Acetate, C30-45 Alkyl Cetearyl Dimethicone Crosspolymer, Stearalkonium Hectorite, Fragrance (Parfum), Xanthan Gum, Betaine, Propylene Carbonate, Disodium EDTA, Laminaria Ochroleuca Extract, Polysorbate 60, Sorbitan Isostearate, Pectin, Sucrose, Glyceryl Acrylate/Acrylic Acid Copolymer, Capryloyl Glycine, Sodium Hyaluronate. 01